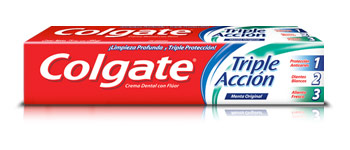 DRUG LABEL: COLGATE TRILPLE ACCION
NDC: 69772-105 | Form: PASTE, DENTIFRICE
Manufacturer: GENESIS IMPORTS & EXPORTS LLC
Category: otc | Type: HUMAN OTC DRUG LABEL
Date: 20170417

ACTIVE INGREDIENTS: SODIUM FLUORIDE 0.32 mg/1 mL
INACTIVE INGREDIENTS: SODIUM LAURYL SULFATE; XANTHAN GUM; GLYCERIN; HYDRATED SILICA; WATER; FD&C BLUE NO. 1; SACCHARIN SODIUM; TITANIUM DIOXIDE; CARBOXYMETHYLCELLULOSE SODIUM, UNSPECIFIED FORM; PIGMENT GREEN 7; EUGENOL

ACTIVE INGREDIENT

Sodium Fluoride .34%

PURPOSE

Anticanity

USE

Helps protect against cavities

KEEP OUT OF REACH OF CHILDREN UNDER 6 YEARS OF AGE. If more that used for brushing is accidentally swallowed, get medical help or contact a poison control center right away.

WARNINGS

Keep outh of the reach of children under 6 years of age. if more than the used for brushing is accidentally swallowed, get medical help or contact a poison control center rigth away

Directions

Adults and children 2 years of age and older: brush teeth thoroughly preferably after each meal or at least twice a day, or as directed by a dentist or physician

Children 2 to 6: use only a pea sized amount and supervise child's brushing and rising (to minimize swallowing)

children under 2 years L ask a dentist or physician

INACTIVE INGREDIENT

water, hydrated silica, blue, sodium lauryl sulfate, cellusosa gum, sacchharin sodium, xanathan gum, titanium dioxide, glycerin, aroma,green #7, eugenol

Directions

Adults and children 2 years of age and older: brush teeth thoroughly preferably after each meal or at least twice a day, or as directed by a dentist or physician

Children 2 to 6: use only a pea sized amount and supervise child's brushing and rising (to minimize swallowing)

children under 2 years L ask a dentist or physician